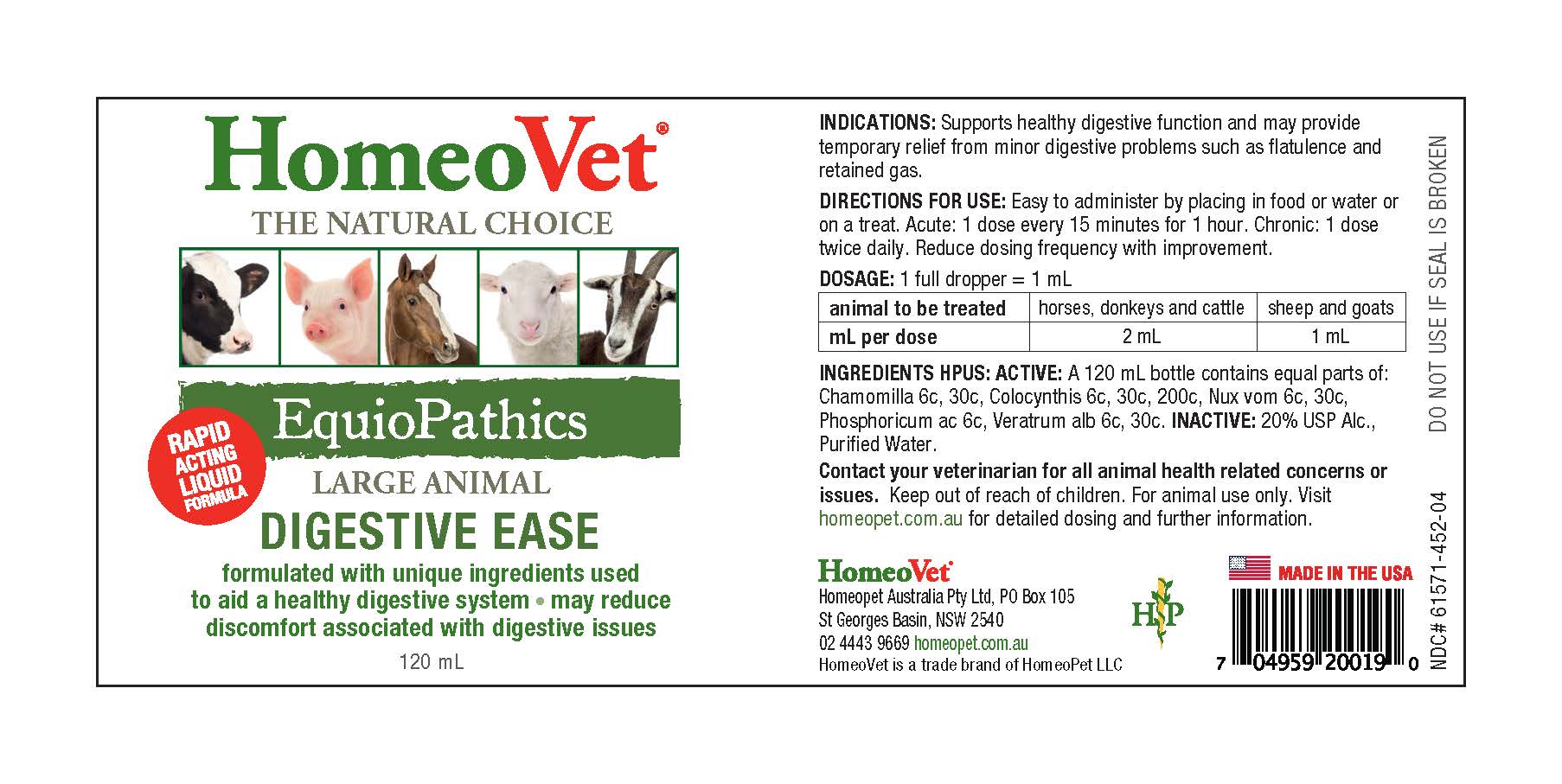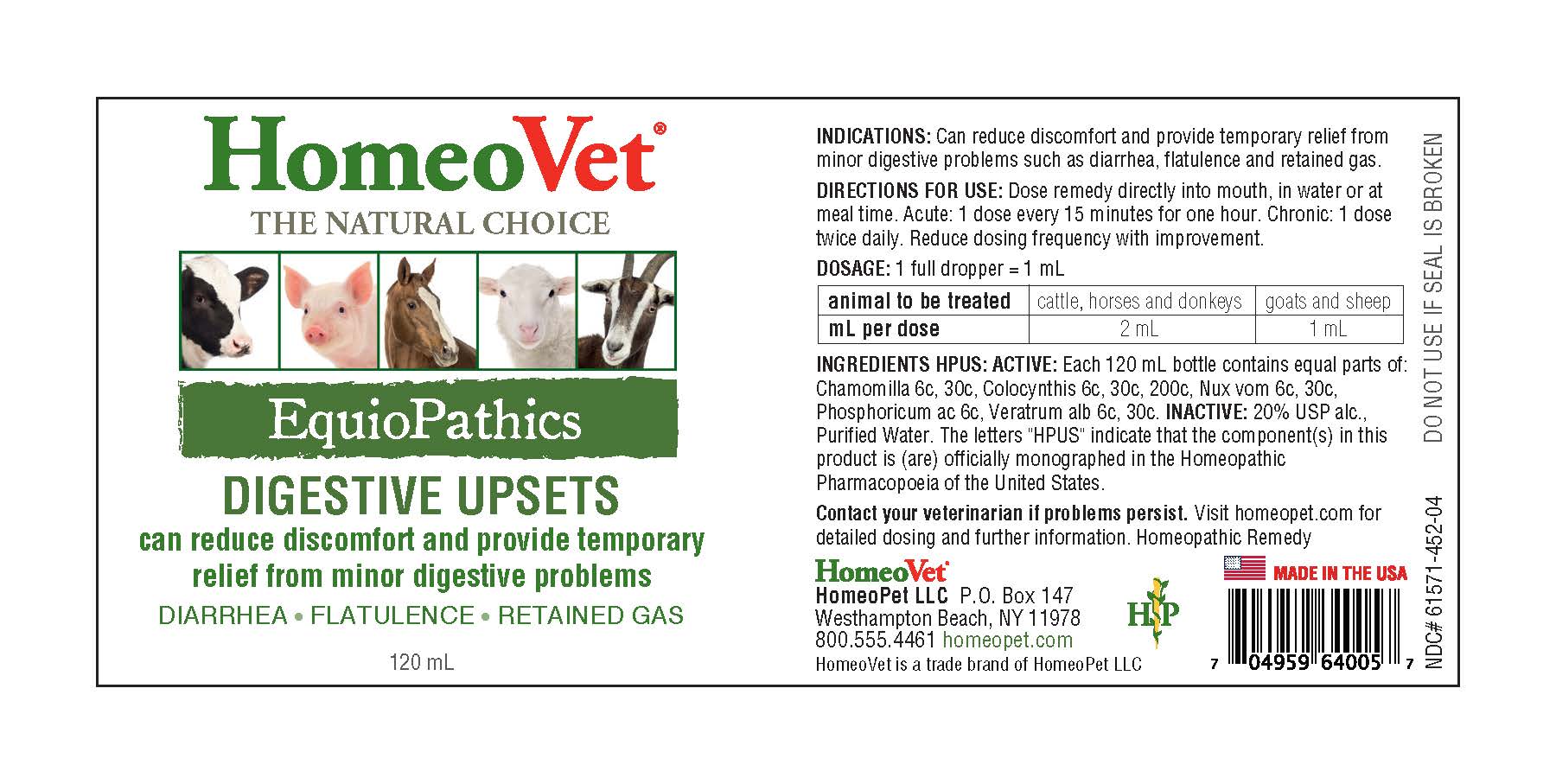 DRUG LABEL: EquioPathics Digestive Upsets
NDC: 61571-452 | Form: LIQUID
Manufacturer: HomeoPet, LLC
Category: homeopathic | Type: OTC ANIMAL DRUG LABEL
Date: 20251211

ACTIVE INGREDIENTS: STRYCHNOS NUX-VOMICA SEED 6 [hp_C]/120 mL; VERATRUM ALBUM ROOT 6 [hp_C]/120 mL; PHOSPHORIC ACID 6 [hp_C]/120 mL; CITRULLUS COLOCYNTHIS FRUIT PULP 6 [hp_C]/120 mL; CHAMOMILE 6 [hp_C]/120 mL
INACTIVE INGREDIENTS: ALCOHOL; WATER

EquioPathics Digestive Upsets

EquioPathics Digestive Upsets

Can reduce discomfort and provide temporary relief from minor digestive problems

DIARRHEA-FLATULENCE-RETAINED GAS

DIRECTIONS FOR USE AND DOSAGE

Dose remedy directly into mouth, in water or at meal time. Acute: 1 dose every 15 minutes for one hour. Chronic: 1dose twice daily. Reduce dosing frequency with improvement.

animal to be treated | cattle, horses and donkeys | goats and sheep
mL per dose | 2 mL | 1 mL

INDICATIONS AND USAGE

Can reduce discomfort and provide temporary relief of minor digestive problems due to diarrhea, flatulence and retained gas.

ACTIVE INGREDIENT

Nux Vomica 6c,30c, Veratrum Album 6c,30c, Phosphoricum Acidum 6c, Colocynthis 6c,30c,200c, Chamomilla 6c,30c

INACTIVE INGREDIENT

Alcohol, Purified Water

ASK DOCTOR

Contact your veterinarian if problems persist.

visit homeopet.com for detailed dosing and further information. Homeopathic Remedy